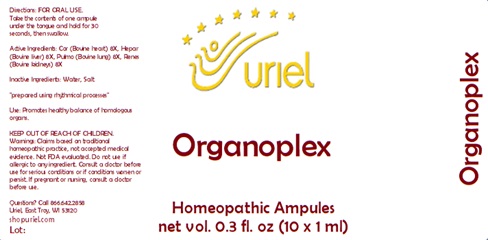 DRUG LABEL: Organoplex
NDC: 48951-7094 | Form: LIQUID
Manufacturer: Uriel Pharmacy Inc.
Category: homeopathic | Type: HUMAN OTC DRUG LABEL
Date: 20240112

ACTIVE INGREDIENTS: BEEF HEART 8 [hp_X]/1 mL; MAMMAL LIVER 8 [hp_X]/1 mL; SUS SCROFA LUNG 8 [hp_X]/1 mL; PORK KIDNEY 8 [hp_X]/1 mL
INACTIVE INGREDIENTS: WATER; SODIUM CHLORIDE

Organoplex

INDICATIONS AND USAGE

Directions: FOR ORAL USE.

DOSAGE AND ADMINISTRATION

Take the contents of one ampule under the tongue and hold for 30 seconds, then swallow.

ACTIVE INGREDIENT

Active Ingredients: Cor (Bovine heart) 8X, Hepar (Bovine liver) 8X, Pulmo (Bovine lung) 8X, Renes (Bovine kidneys) 8X

Inactive Ingredients: Water, Salt

"prepared using rhythmical processes"

PURPOSE

Use: Promotes healthy balance of homologous organs.

KEEP OUT OF REACH OF CHILDREN.

WARNINGS

Warnings: Claims based on traditional homeopathic practice, not accepted medical evidence. Not FDA evaluated. Do not use if allergic to any ingredient. Consult a doctor before use for serious conditions or if conditions worsen or persist. If pregnant or nursing, consult a doctor before use.

QUESTIONS

Questions? Call 866.642.2858 Uriel, East Troy, WI 53120 shopuriel.com